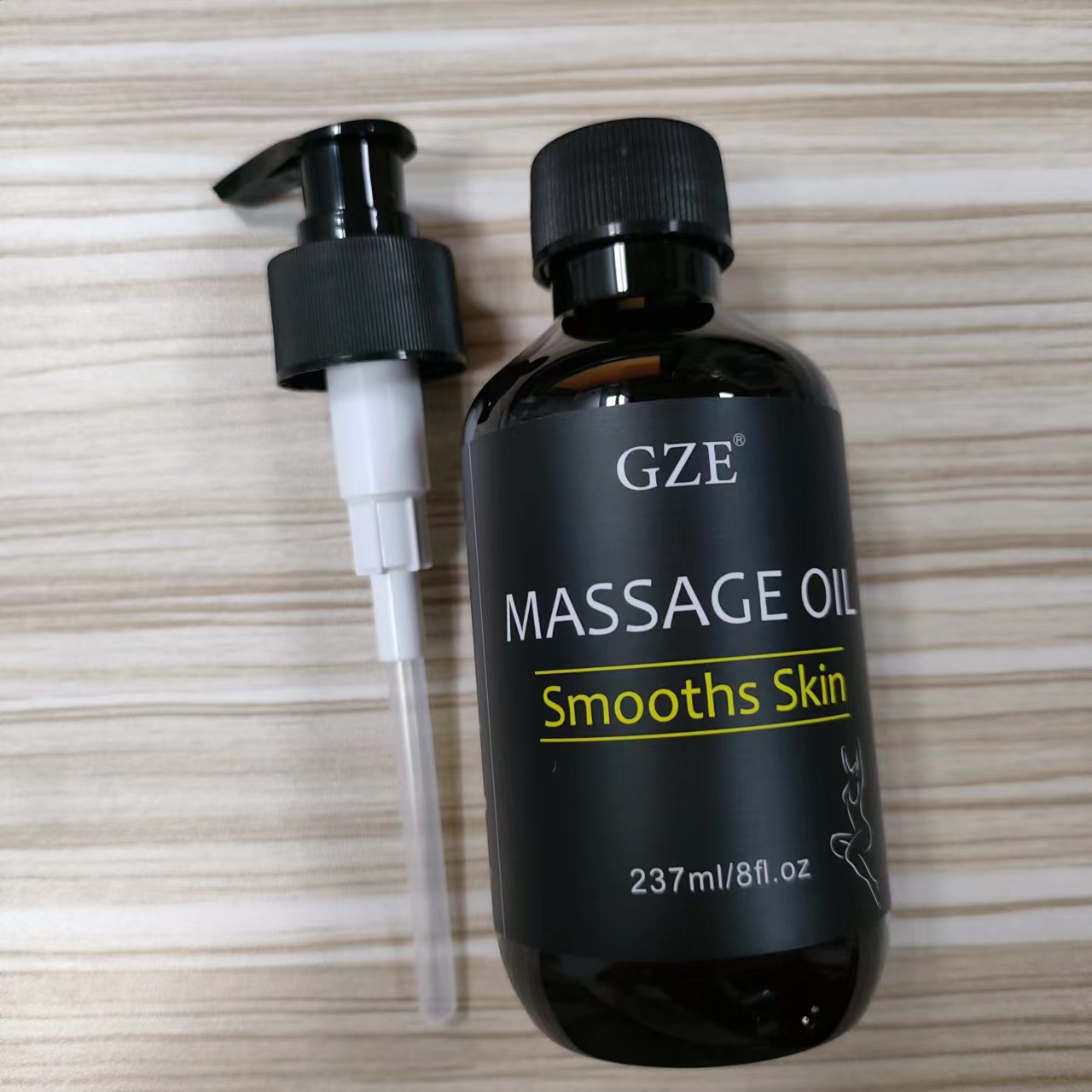 DRUG LABEL: GZE Massage Oil
NDC: 74458-099 | Form: OIL
Manufacturer: Guangzhou Yilong Cosmetics Co., Ltd
Category: otc | Type: HUMAN OTC DRUG LABEL
Date: 20241030

ACTIVE INGREDIENTS: CITRUS PARADISI (GRAPEFRUIT) PEEL OIL 10 g/100 mL; SIMMONDSIA CHINENSIS (JOJOBA) SEED OIL 10.3 g/100 mL; CITRUS AURANTIUM BERGAMIA (BERGAMOT) FRUIT OIL 10 g/100 mL; EUCALYPTOL 4.55 g/100 mL; OLEA EUROPAEA (OLIVE) FRUIT OIL 21.3 g/100 mL; PRUNUS AMYGDALUS DULCIS (SWEET ALMOND) OIL 43.45 g/100 mL
INACTIVE INGREDIENTS: TOCOPHEROL

GZE MASSAGE OIL

ACTIVE INGREDIENT

Prunus Amygdalus Dulcis (Sweet Almond) Seed Oil 43.45%
Olea Europaea (Olive) Fruit Oil 21.3%
Simmondsia Chinensis (Jojoba) Seed Oil 10.3%
Citrus Paradisi (Grapefruit) Peel Oil 10%
Citrus Aurantium Bergamia (Bergamot) Fruit Oil 10%
Eucalyptol 4.55%

INACTIVE INGREDIENT

Tocopherol

INDICATIONS AND USAGE

Apply the massage oil on damp skin after taking a shower or bath as this will lock in the moisture. Massage the oil into skin until it is absorbed.

PURPOSE

Moisturizing

WARNINGS

For external use only.

Stop use and ask a doctor if rash occurs.

Do not use on damaged or broken skin.

When using this product keep out of eyes. Rinse with water to remove.

Keep out of reach of children. If swallowed, get medical help or contact a Poison Control Center right away.

DOSAGE AND ADMINISTRATION

Apply the massage oil on damp skin after taking a shower or bath as this will lock in the moisture. Massage the oil into skin until it is absorbed.